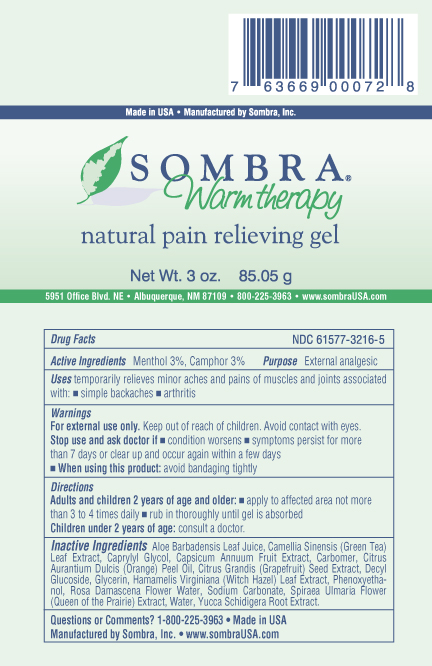 DRUG LABEL: SOMBRA WARM THERAPY
NDC: 61577-3636 | Form: CREAM
Manufacturer: SOMBRA COSMETICS INC.
Category: otc | Type: HUMAN OTC DRUG LABEL
Date: 20260225

ACTIVE INGREDIENTS: CAMPHOR (SYNTHETIC) 0.03 g/1 g; MENTHOL 0.03 g/1 g
INACTIVE INGREDIENTS: ALOE VERA LEAF; CARBOMER HOMOPOLYMER TYPE C; DECYL GLUCOSIDE; WATER; CAPSAICIN; GRAPEFRUIT SEED OIL; GREEN TEA LEAF; FILIPENDULA ULMARIA FLOWER; ROSA CENTIFOLIA FLOWER OIL; SODIUM CARBONATE; GLYCERIN; WITCH HAZEL; YUCCA SCHIDIGERA ROOT; ORANGE PEEL; PHENOXYETHANOL; CAPRYLYL GLYCOL

ScripHessco Warm Therapy Pain Relief

Active Ingredients

Menthol USP 3%, Camphor USP 3%

Purpose

External Analgesic

Keep out of reach of children

Uses

Temporarily relieves minor aches and pains of muscles and joints associated with: arthritis, simple backaches

Warnings

For external use only. Do not use on wounds or damaged skin. When using this product: avoid bandaging tightly, avoid contact with eyes, keep out of reach of children.

Stop use and ask doctor if: condition worsens, symptoms persist for more than 7 days, clear up and occur again within a few days.

Directions

adults and children 2 years of age and older: apply to affected area not more than 3 to 4 times daily, rub in thoroughly until gel is absorbed, children under 2 years of age: consult a doctor.

Inactive Ingredients

aloe barbadensis leaf juice, carbomer, decyl glucoside, water, citrus grandis (grapefruit) seed extract, camellia sinensis (green tea) leaf extract, citrus aurantium dulcis (orange) peel oil, spiraea ulmaria flower (queen of the prairie) extract, rosa damascena flower water, sodium carbonate, glycerin, hamamelis virginiana (witch hazel) leaf extract, yucca schidigera root extract, phenoxyethanol, caprylyl glycol, capsicum annuum fruit extract

Questions or Comments

1-800-225-3963